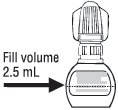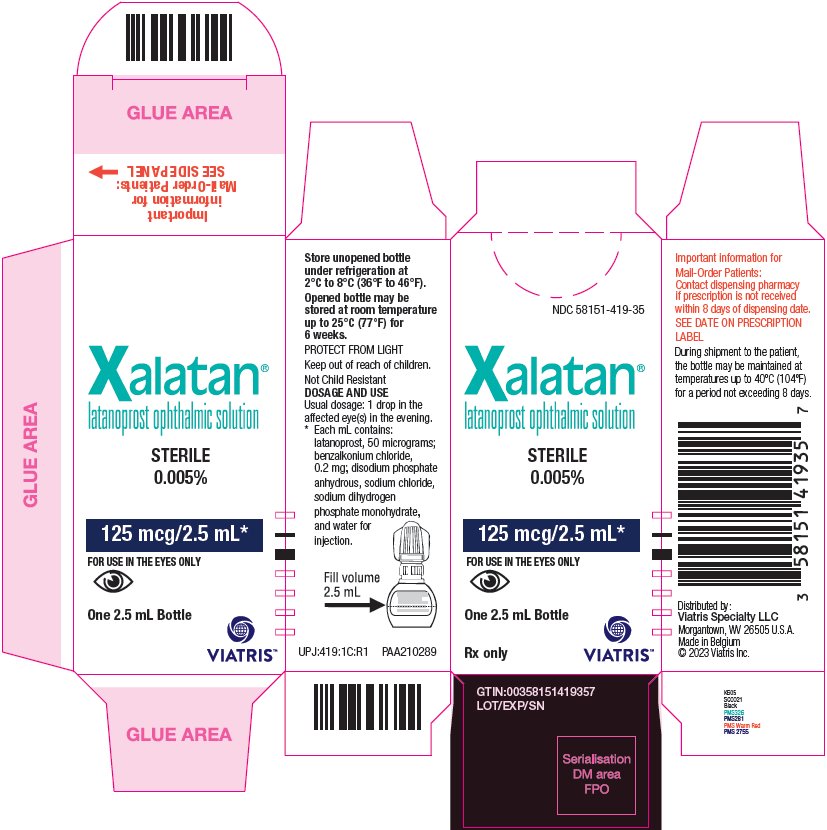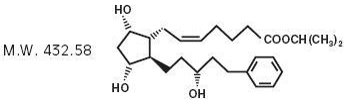 DRUG LABEL: XALATAN
NDC: 58151-419 | Form: SOLUTION/ DROPS
Manufacturer: Viatris Specialty LLC
Category: prescription | Type: HUMAN PRESCRIPTION DRUG LABEL
Date: 20230515

ACTIVE INGREDIENTS: LATANOPROST 50 ug/1 mL
INACTIVE INGREDIENTS: SODIUM PHOSPHATE, DIBASIC, ANHYDROUS; SODIUM CHLORIDE; WATER; SODIUM PHOSPHATE, MONOBASIC, MONOHYDRATE

HIGHLIGHTS OF PRESCRIBING INFORMATION

These highlights do not include all the information needed to use XALATAN safely and effectively. See full prescribing information for XALATAN.
XALATAN® (latanoprost ophthalmic solution) 0.005%, for topical ophthalmic use
Initial U.S. Approval: 1996

1 INDICATIONS AND USAGE

XALATAN is a prostaglandin F2α analogue indicated for the reduction of elevated intraocular pressure in patients with open-angle glaucoma or ocular hypertension. (1)

2 DOSAGE AND ADMINISTRATION

One drop in the affected eye(s) once daily in the evening. (2)

3 DOSAGE FORMS AND STRENGTHS

Ophthalmic solution containing latanoprost 50 mcg/mL (0.005%). (3)

4 CONTRAINDICATIONS

Known hypersensitivity to latanoprost, benzalkonium chloride, or any other ingredients in this product. (4)

5 WARNINGS AND PRECAUTIONS

- Pigmentation: Pigmentation of the iris, periorbital tissue (eyelid) and eyelashes can occur. Iris pigmentation likely to be permanent. (5.1)
- Eyelash Changes: Gradual change to eyelashes including increased length, thickness and number of lashes. Usually reversible. (5.2)

6 ADVERSE REACTIONS

Most common adverse reactions (5-15%) from clinical trials are blurred vision, burning and stinging, conjunctival hyperemia, foreign body sensation, itching, increased pigmentation of the iris, and punctate keratitis. (6)

To report SUSPECTED ADVERSE REACTIONS, contact Viatris at 1-877-446-3679 (1-877-4-INFO-RX) or FDA at 1-800-FDA-1088 or www.fda.gov/medwatch.

FULL PRESCRIBING INFORMATION

1 INDICATIONS AND USAGE

XALATAN is indicated for the reduction of elevated intraocular pressure (IOP) in patients with open-angle glaucoma or ocular hypertension.

2 DOSAGE AND ADMINISTRATION

The recommended dosage is one drop in the affected eye(s) once daily in the evening. If one dose is missed, treatment should continue with the next dose as normal.

The dosage of XALATAN should not exceed once daily; the combined use of two or more prostaglandins, or prostaglandin analogs including XALATAN is not recommended. It has been shown that administration of these prostaglandin drug products more than once daily may decrease the IOP lowering effect or cause paradoxical elevations in IOP.

Reduction of the IOP starts approximately 3 to 4 hours after administration and the maximum effect is reached after 8 to 12 hours.

XALATAN may be used concomitantly with other topical ophthalmic drug products to lower IOP. In vitro studies have shown that precipitation occurs when eye drops containing thimerosal are mixed with XALATAN. If more than one topical ophthalmic drug is being used, the drugs should be administered at least five (5) minutes apart. Contact lenses should be removed prior to the administration of XALATAN, and may be reinserted 15 minutes after administration.

3 DOSAGE FORMS AND STRENGTHS

Ophthalmic solution containing latanoprost 50 mcg/mL (0.005%).

4 CONTRAINDICATIONS

Known hypersensitivity to latanoprost, benzalkonium chloride, or any other ingredients in this product.

5 WARNINGS AND PRECAUTIONS

5.1 Pigmentation

XALATAN has been reported to cause changes to pigmented tissues. The most frequently reported changes have been increased pigmentation of the iris, periorbital tissue (eyelid), and eyelashes. Pigmentation is expected to increase as long as latanoprost is administered.

The pigmentation change is due to increased melanin content in the melanocytes rather than to an increase in the number of melanocytes. After discontinuation of latanoprost, pigmentation of the iris is likely to be permanent, while pigmentation of the periorbital tissue and eyelash changes have been reported to be reversible in some patients. Patients who receive treatment should be informed of the possibility of increased pigmentation. Beyond 5 years the effects of increased pigmentation are not known [see Clinical Studies (14.2)].

Iris color change may not be noticeable for several months to years. Typically, the brown pigmentation around the pupil spreads concentrically towards the periphery of the iris and the entire iris or parts of the iris become more brownish. Neither nevi nor freckles of the iris appear to be affected by treatment. While treatment with XALATAN can be continued in patients who develop noticeably increased iris pigmentation, these patients should be examined regularly.

5.2 Eyelash Changes

XALATAN may gradually change eyelashes and vellus hair in the treated eye; these changes include increased length, thickness, pigmentation, the number of lashes or hairs, and misdirected growth of eyelashes. Eyelash changes are usually reversible upon discontinuation of treatment.

5.3 Intraocular Inflammation

XALATAN should be used with caution in patients with a history of intraocular inflammation (iritis/uveitis) and should generally not be used in patients with active intraocular inflammation because inflammation may be exacerbated.

5.4 Macular Edema

Macular edema, including cystoid macular edema, has been reported during treatment with XALATAN. XALATAN should be used with caution in aphakic patients, in pseudophakic patients with a torn posterior lens capsule, or in patients with known risk factors for macular edema.

5.5 Herpetic Keratitis

Reactivation of herpes simplex keratitis has been reported during treatment with XALATAN. XALATAN should be used with caution in patients with a history of herpetic keratitis. XALATAN should be avoided in cases of active herpes simplex keratitis because inflammation may be exacerbated.

5.6 Bacterial Keratitis

There have been reports of bacterial keratitis associated with the use of multiple-dose containers of topical ophthalmic products. These containers had been inadvertently contaminated by patients who, in most cases, had a concurrent corneal disease or a disruption of the ocular epithelial surface.

5.7 Contact Lens Use

XALATAN contains benzalkonium chloride, which may be absorbed by contact lenses. Contact lenses should be removed prior to the administration of XALATAN, and may be reinserted 15 minutes after administration.

6 ADVERSE REACTIONS

The following adverse reactions were reported in postmarketing experience and are discussed in greater detail in other sections of the label:

- Iris pigmentation changes [see Warnings and Precautions (5.1)]
- Eyelid skin darkening [see Warnings and Precautions (5.1)]
- Eyelash changes (increased length, thickness, pigmentation, and number of lashes) [see Warnings and Precautions (5.2)]
- Intraocular inflammation (iritis/uveitis) [see Warnings and Precautions (5.3)]
- Macular edema, including cystoid macular edema [see Warnings and Precautions (5.4)]

6.1 Clinical Trials Experience

Because clinical trials are conducted under widely varying conditions, the adverse reaction rates observed in the clinical studies of a drug cannot be directly compared to rates in the clinical trials of another drug and may not reflect the rates observed in clinical practice.

XALATAN was studied in three multicenter, randomized, controlled clinical trials. Patients received 50 mcg/mL XALATAN once daily or 5 mg/mL active-comparator (timolol) twice daily. The patient population studied had a mean age of 65±10 years. Seven percent of patients withdrew before the 6-month endpoint.

Table 1: Ocular Adverse Reactions and Ocular Signs/Symptoms Reported by 5-15% of Patients Receiving Latanoprost
Symptom/Finding | Adverse Reactions (Incidence (%))
Symptom/Finding | Latanoprost; (n=460) | Timolol; (n=369)
Foreign body sensation | 13 | 8
Punctate keratitis | 10 | 9
Stinging | 9 | 12
Conjunctival hyperemia | 8 | 3
Blurred vision | 8 | 8
Itching | 8 | 8
Burning | 7 | 8
Increased pigmentation of the iris | 7 | 0

Less than 1% of the patients treated with XALATAN required discontinuation of therapy because of intolerance to conjunctival hyperemia.

Table 2: Adverse Reactions That Were Reported in 1-5% of Patients Receiving Latanoprost
 | Adverse Reactions (Incidence (%))
 | Latanoprost; (n=460) | Timolol; (n=369)
Ocular Events/Signs and Symptoms
Excessive tearing | 4 | 6
Eyelid discomfort/pain | 4 | 2
Dry eye | 3 | 3
Eye pain | 3 | 3
Eyelid margin crusting | 3 | 3
Erythema of the eyelid | 3 | 2
Photophobia | 2 | 1
Eyelid edema | 1 | 3
Blepharitis | 1 | 3
Systemic Events
Upper respiratory tract infection/nasopharyngitis/influenza | 3 | 3
Myalgia/arthralgia/back pain | 1 | 0.5
Rash/allergic skin reaction | 1 | 0.3

6.2 Postmarketing Experience

The following reactions have been identified during postmarketing use of XALATAN in clinical practice. Because they are reported voluntarily from a population of unknown size, it is not always possible to reliably estimate their frequency or establish a causal relationship to drug exposure. The reactions, which have been chosen for inclusion due to either their seriousness, frequency of reporting, possible causal connection to XALATAN, or a combination of these factors, include:

Nervous System Disorders: Dizziness; headache; toxic epidermal necrolysis

Eye Disorders: Eyelash and vellus hair changes of the eyelid (increased length, thickness, pigmentation, and number of eyelashes); keratitis; corneal edema and erosions; intraocular inflammation (iritis/uveitis); macular edema, including cystoid macular edema; trichiasis; periorbital and lid changes resulting in deepening of the eyelid sulcus; iris cyst; eyelid skin darkening; localized skin reaction on the eyelids; conjunctivitis; pseudopemphigoid of the ocular conjunctiva.

Respiratory, Thoracic and Mediastinal Disorders: Asthma and exacerbation of asthma; dyspnea

Gastrointestinal Disorders: Nausea; vomiting

Skin and Subcutaneous Tissue Disorders: Pruritis

Infections and Infestations: Herpes keratitis

Cardiac Disorders: Angina; palpitations; angina unstable

General Disorders and Administration Site Conditions: Chest pain

8 USE IN SPECIFIC POPULATIONS

8.1 Pregnancy

Risk Summary

There are no adequate and well-controlled studies of XALATAN administration in pregnant women to inform drug-associated risks.

In animal reproduction studies, intravenous (IV) administration of latanoprost to pregnant rabbits and rats throughout the period of organogenesis produced malformations, embryofetal lethality and spontaneous abortion at clinically relevant doses [see Data].

The background risk of major birth defects and miscarriage for the indicated population is unknown. However, the background risk in the U.S. general population of major birth defects is 2 to 4%, and of miscarriage is 15 to 20% of clinically recognized pregnancies.

Data

Animal Data

Embryofetal studies were conducted in pregnant rabbits administered latanoprost daily by IV injection on gestation days 6 through 18, to target the period of organogenesis. A no observed adverse effect level (NOAEL) was not established for rabbit developmental toxicity. Post-implantation loss due to late resorption was shown as doses ≥0.2 mcg/kg/day (equivalent to 1.3 times the maximum recommended human ophthalmic dose [RHOD], on a mg/m^2 basis, assuming 100% absorption). Spina bifida and abortion occurred at 5 mcg/kg/day (equivalent to 32 times the maximum RHOD). Total litter loss due to early resorption was observed at doses ≥50 mcg/kg/day (324 times the maximum RHOD). Transient signs of maternal toxicity were observed after IV dosing (increased breathing, muscle tremors, slight motor incoordination) at 300 mcg/kg/day (1946 times the maximum RHOD). No maternal toxicity was observed at doses up to 50 mcg/kg/day.

Embryofetal studies were conducted in pregnant rats administered latanoprost daily by IV injection on gestation days 6 through 15, to target the period of organogenesis. A NOAEL for rat developmental toxicity was not established. Cleft palate was observed at 1 mcg/kg (equivalent to 3.2 times the maximum RHOD, on a mg/m^2 basis, assuming 100% absorption). Brain porencephalic cyst(s) were observed ≥50 mcg/kg (162 times the maximum RHOD). Skeletal anomalies were observed at 250 mcg/kg (811 times the maximum RHOD). No maternal toxicity was detectable at 250 mcg/kg/day.

Prenatal and postnatal development was assessed in rats. Pregnant rats were administered latanoprost daily by IV injection from gestation day 15, through delivery, until weaning (lactation day 21). No adverse effects on rat offspring were observed at doses up to 10 mcg/kg/day (32 times the maximum RHOD, on a mg/m^2 basis, assuming 100% absorption). At 100 mcg/kg/day (324 times the maximum RHOD), maternal deaths and pup mortality occurred.

8.2 Lactation

Risk Summary

It is not known whether this drug or its metabolites are excreted in human milk. Because many drugs are excreted in human milk, caution should be exercised when XALATAN is administered to a nursing woman.

The developmental and health benefits of breastfeeding should be considered along with the mother’s clinical need for XALATAN and any potential adverse effects on the breastfed child from XALATAN.

8.4 Pediatric Use

Safety and effectiveness in pediatric patients have not been established.

8.5 Geriatric Use

No overall differences in safety or effectiveness have been observed between elderly and younger patients.

10 OVERDOSAGE

IV infusion of up to 3 mcg/kg of latanoprost in healthy volunteers produced mean plasma concentrations 200 times higher than during clinical treatment with XALATAN and no adverse reactions were observed. IV dosages of 5.5 to 10 mcg/kg caused abdominal pain, dizziness, fatigue, hot flushes, nausea, and sweating.

If overdosage with XALATAN occurs, treatment should be symptomatic.

11 DESCRIPTION

Latanoprost is a prostaglandin F2α analogue. Its chemical name is isopropyl-(Z)-7[(1R,2R,3R,5S)3,5-dihydroxy-2-[(3R)-3-hydroxy-5-phenylpentyl]cyclopentyl]-5-heptenoate. Its molecular formula is C26H40O5 and its chemical structure is:

Latanoprost is a colorless to slightly yellow oil that is very soluble in acetonitrile and freely soluble in acetone, ethanol, ethyl acetate, isopropanol, methanol, and octanol. It is practically insoluble in water.

XALATAN (latanoprost ophthalmic solution) 0.005% is supplied as a sterile, isotonic, buffered aqueous solution of latanoprost with a pH of approximately 6.7 and an osmolality of approximately 267 mOsmol/kg. Each mL of XALATAN contains 50 mcg of latanoprost. Benzalkonium chloride, 0.02% is added as a preservative. The inactive ingredients are disodium phosphate anhydrous, sodium chloride, sodium dihydrogen phosphate monohydrate, and water for injection. One drop contains approximately 1.5 mcg of latanoprost.

12 CLINICAL PHARMACOLOGY

12.1 Mechanism of Action

Latanoprost is a prostaglandin F2α analogue that is believed to reduce the IOP by increasing the outflow of aqueous humor. Studies in animals and man suggest that the main mechanism of action is increased uveoscleral outflow. Elevated IOP represents a major risk factor for glaucomatous field loss. The higher the level of IOP, the greater the likelihood of optic nerve damage and visual field loss.

12.2 Pharmacodynamics

Reduction of the IOP in man starts about 3-4 hours after administration and maximum effect is reached after 8-12 hours. IOP reduction is present for at least 24 hours.

12.3 Pharmacokinetics

Absorption

Latanoprost is absorbed through the cornea where the isopropyl ester prodrug is hydrolyzed to the acid form to become biologically active.

Distribution

The distribution volume in humans is 0.16±0.02 L/kg. The acid of latanoprost can be measured in aqueous humor during the first 4 hours, and in plasma only during the first hour after local administration. Studies in man indicate that the peak concentration in the aqueous humor is reached about 2 hours after topical administration.

Elimination

Metabolism

Latanoprost, an isopropyl ester prodrug, is hydrolyzed by esterases in the cornea to the biologically active acid. The active acid of latanoprost reaching the systemic circulation is primarily metabolized by the liver to the 1,2-dinor and 1,2,3,4-tetranor metabolites via fatty acid β-oxidation.

Excretion

The elimination of the acid of latanoprost from human plasma is rapid (t1/2 = 17 min) after both IV and topical administration. Systemic clearance is approximately 7 mL/min/kg. Following hepatic β-oxidation, the metabolites are mainly eliminated via the kidneys. Approximately 88% and 98% of the administered dose are recovered in the urine after topical and IV dosing, respectively.

13 NONCLINICAL TOXICOLOGY

13.1 Carcinogenesis, Mutagenesis, Impairment of Fertility

Carcinogenesis

Latanoprost was not carcinogenic in either mice or rats when administered by oral gavage at doses of up to 170 mcg/kg/day (approximately 2800 times the recommended maximum human dose) for up to 20 and 24 months, respectively.

Mutagenesis

Latanoprost was not mutagenic in bacteria, in mouse lymphoma, or in mouse micronucleus tests. Chromosome aberrations were observed in vitro with human lymphocytes. Additional in vitro and in vivo studies on unscheduled DNA synthesis in rats were negative.

Impairment of Fertility

Latanoprost has not been found to have any effect on male or female fertility in rat studies at IV doses up to 250 mcg/kg/day (811 times the maximum RHOD, on a mg/m^2 basis, assuming 100% absorption).

14 CLINICAL STUDIES

14.1 Elevated Baseline IOP

Patients with mean baseline IOP of 24-25 mmHg who were treated for 6 months in multi-center, randomized, controlled trials demonstrated 6-8 mmHg reductions in IOP. This IOP reduction with XALATAN 0.005% dosed once daily was equivalent to the effect of timolol 0.5% dosed twice daily.

14.2 Progression of Increased Iris Pigmentation

A 3-year open-label, prospective safety study with a 2-year extension phase was conducted to evaluate the progression of increased iris pigmentation with continuous use of XALATAN once-daily as adjunctive therapy in 519 patients with open-angle glaucoma. The analysis was based on observed-cases population of the 380 patients who continued in the extension phase.

Results showed that the onset of noticeable increased iris pigmentation occurred within the first year of treatment for the majority of the patients who developed noticeable increased iris pigmentation. Patients continued to show signs of increasing iris pigmentation throughout the 5 years of the study. Observation of increased iris pigmentation did not affect the incidence, nature, or severity of adverse events (other than increased iris pigmentation) recorded in the study. IOP reduction was similar regardless of the development of increased iris pigmentation during the study.

16 HOW SUPPLIED/STORAGE AND HANDLING

XALATAN is a clear, isotonic, buffered, preserved colorless solution of latanoprost 50 mcg/mL (0.005%). It is supplied as a 2.5 mL solution in a 5 mL clear low density polyethylene bottle with a clear polyethylene dropper tip, a turquoise high density polyethylene screw cap, and a tamper-evident clear low density polyethylene overcap.

2.5 mL fill, 50 mcg/mL (0.005%): Package of 1 bottle: NDC 58151-419-35

Storage: Protect from light. Store unopened bottle(s) under refrigeration at 2°C to 8°C (36°F to 46°F). During shipment to the patient, the bottle may be maintained at temperatures up to 40°C (104°F) for a period not exceeding 8 days. Once a bottle is opened for use, it may be stored at room temperature up to 25°C (77°F) for 6 weeks.

17 PATIENT COUNSELING INFORMATION

Potential for Pigmentation

Advise patients about the potential for increased brown pigmentation of the iris, which may be permanent. Inform patients about the possibility of eyelid skin darkening, which may be reversible after discontinuation of XALATAN [see Warnings and Precautions (5.1)].

Potential for Eyelash Changes

Inform patients of the possibility of eyelash and vellus hair changes in the treated eye during treatment with XALATAN. These changes may result in a disparity between eyes in length, thickness, pigmentation, number of eyelashes or vellus hairs, and/or direction of eyelash growth. Eyelash changes are usually reversible upon discontinuation of treatment.

Handling the Container

Instruct patients to avoid allowing the tip of the dispensing container to contact the eye or surrounding structures because this could cause the tip to become contaminated by common bacteria known to cause ocular infections. Serious damage to the eye and subsequent loss of vision may result from using contaminated solutions [see Warnings and Precautions (5.6)].

When to Seek Physician Advice

Advise patients that if they develop an intercurrent ocular condition (e.g., trauma or infection) or have ocular surgery, or develop any ocular reactions, particularly conjunctivitis and eyelid reactions, they should immediately seek their physician’s advice concerning the continued use of the multiple-dose container.

Contact Lens Use

Advise patients that XALATAN contains benzalkonium chloride, which may be absorbed by contact lenses. Contact lenses should be removed prior to administration of the solution. Lenses may be reinserted 15 minutes following administration of XALATAN.

Use with Other Ophthalmic Drugs

Advise patients that if more than one topical ophthalmic drug is being used, the drugs should be administered at least five (5) minutes apart.

If a Dose is Missed

Advise patients that if one dose is missed, treatment should continue with the next dose as normal.

Distributed by:
Viatris Specialty LLC
Morgantown, WV 26505 U.S.A.

Made in Belgium

© 2023 Viatris Inc.

XALATAN is a registered trademark of Pfizer PFE Holdings 4 LLC, a Viatris Company.

UPJ:XLTN:R1

PRINCIPAL DISPLAY PANEL – 0.005%

NDC 58151-419-35

Xalatan®
latanoprost ophthalmic solution
STERILE
0.005%

125 mcg/2.5 mL*

FOR USE IN THE EYES ONLY

One 2.5 mL Bottle

Rx only

Store unopened bottle
under refrigeration at
2°C to 8°C (36°F to 46°F).

Opened bottle may be
stored at room temperature
up to 25°C (77°F) for
6 weeks.

PROTECT FROM LIGHT

Keep out of reach of children.

Not Child Resistant

DOSAGE AND USE
Usual dosage: 1 drop in the
affected eye(s) in the evening.

* Each mL contains:
latanoprost, 50 micrograms;
benzalkonium chloride,
0.2 mg; disodium phosphate
anhydrous, sodium chloride,
sodium dihydrogen
phosphate monohydrate,
and water for
injection.

UPJ:419:1C:R1 PAA210289

Important information for
Mail-Order Patients:
Contact dispensing pharmacy
if prescription is not received
within 8 days of dispensing date.

SEE DATE ON PRESCRIPTION
LABEL

During shipment to the patient,
the bottle may be maintained at
temperatures up to 40ºC (104ºF)
for a period not exceeding 8 days.

Distributed by:
Viatris Specialty LLC
Morgantown, WV 26505 U.S.A.

Made in Belgium

© 2023 Viatris Inc.